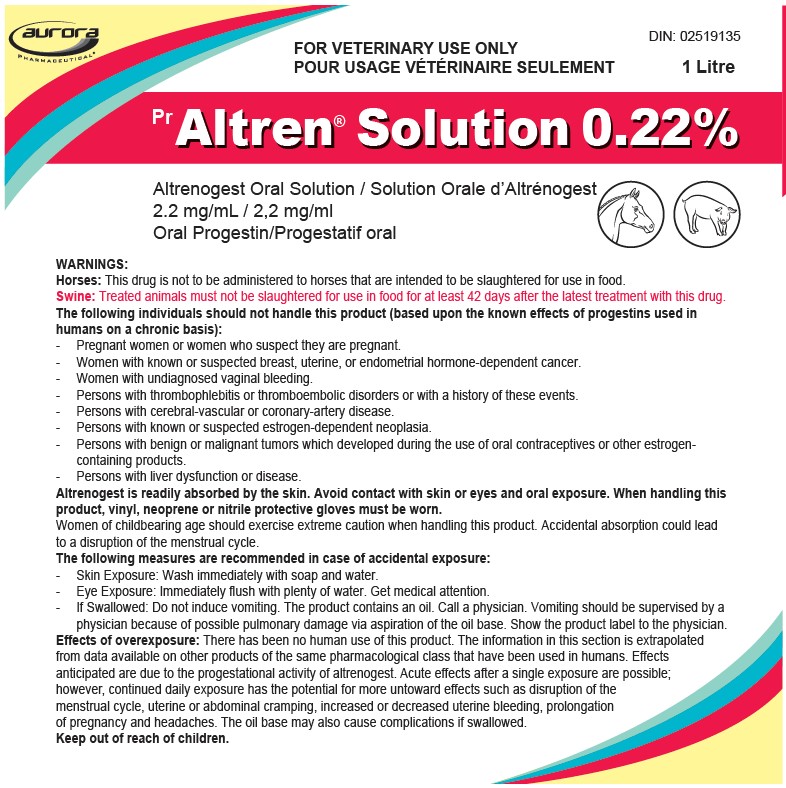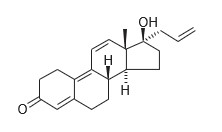 DRUG LABEL: Altren
NDC: 51072-108 | Form: SOLUTION
Manufacturer: Aurora Pharmaceutical, Inc.
Category: animal | Type: PRESCRIPTION ANIMAL DRUG LABEL
Date: 20241009

ACTIVE INGREDIENTS: ALTRENOGEST 2.2 mg/1 mL

Altren® Solution 0.22%
(altrenogest)

DOSAGE FORMS AND STRENGTHS

2.2 mg/mL

ORAL PROGESTIN

DESCRIPTION:

Altren® (altrenogest) Solution 0.22% contains the active synthetic progestin, altrenogest. The chemical name is 17α-allyl-17β-hydroxyestra-4,9,11-trien-3-one. The CAS Registry Number is 850-52-2. The chemical structure is:

Each mL of Altren® (altrenogest) Solution 0.22% contains 2.2 mg of altrenogest in an oil solution.

THERAPEUTIC CLASSIFICATION:

Altren® Solution 0.22% produces a progestational effect in mares and gilts.

INDICATIONS:

Horses: Altren® Solution 0.22% is indicated for suppression of estrus. Suppression of estrus allows for a predictable occurrence of estrus following drug withdrawal. This facilitates the attainment of regular cyclicity during the transition from winter anestrus to the physiological breeding season. Suppression of estrus will also facilitate management of prolonged estrus conditions. Suppression of estrus may be used to facilitate scheduled breeding during the physiological breeding season.

Swine: Altren® Solution 0.22% is indicated for suppression of estrus in sexually mature gilts.
Altren® Solution 0.22% mimics the action of progesterone and blocks the cyclical release of gonadotrophins and thus the development of estrus. Following cessation of
treatment, pituitary inhibition ceases and normal development and maturation of the follicles returns, leading to a return to estrus and ovulation. The predictable return to estrus (generally 5-7 days following cessation of treatment) allows for estrus synchronization in a pool of cycling gilts.

Altren® Solution 0.22% is indicated for suppression of estrus in sexually mature gilts to:
1. Permit synchronization of estrus in cycling gilts.
2. Improve breeding unit organization by facilitating batch management (all in, all out system) of the breeding gilts.
3. Reduce the pre-breeding gilt pool size.

DOSAGE AND ADMINISTRATION:

Horses: Administer orally at the rate of 1 ml per 50kg (110 lbs) body weight (0.044mg/kg) once daily for 15 consecutive days. Administer orally by dose syringe or suitable plastic syringe on to the posterior-dorsal surface of the tongue. The recommended dose may alternatively be added to the usual ration.

Dosage Chart:

Approximate Weight | Dose
in Pounds | in mL
770 | 7
880 | 8
990 | 9
1100 | 10
1210 | 11
1320 | 12

Extensive clinical trials have demonstrated that estrus will be suppressed in approximately 95% of the mares within three days; however, the post-treatment response depends on the level of ovarian activity when treatment was initiated. Estrus in mares exhibiting regular estrus cycles during the breeding season will be suppressed during treatment; these mares return to estrus four or five days following treatment and continue to cycle normal estrus following withdrawal.

Response in mares in the transition phase between winter anestrus and the summer breeding season depends on the degree of follicular activity. Mares with inactive ovaries and small follicles failed to respond with normal cycles post-treatment.

DOSAGE AND ADMINISTRATION

Swine: Top dress on gilts daily ration at the rate of 15mg of altrenogest per gilt per day for 14 consecutive days. The recommended daily dose represents 6.8 mL of the 0.22% solution.

SPECIFIC USES FOR ALTREN® SOLUTION 0.22%:

Horses: Suppression of estrus to:
1. Facilitate attainment of regular cycles during the transition period from winter anestrus to the physiological breeding season.
To facilitate the attainment of regular cycles during the transition phase, mares should be examined to determine the degree of ovarian activity. Estrus in mares with inactive ovaries (no follicles greater than 20 mm in diameter) will be suppressed but these mares may not begin regular cycles following treatment. However, mares with active ovaries (follicles greater than 20 mm in diameter) frequently respond with regular post-treatment estrus cycles.

2. Facilitate management of the mares exhibiting prolonged estrus during the transition period. Estrus will be suppressed in mares exhibiting prolonged behavioural estrus either early or later during the transition period. Again, the post-treatment response depends upon the level of ovarian activity. The mares with greater ovarian activity initiate regular cycles and conceive sooner than the inactive mares. Altren® Solution 0.22% may be administered early in the transition period to suppress estrus in mares with inactive ovaries to aid in the management of these mares or to mares later in the transition period with active ovaries to prepare and schedule the mare for breeding.

3. Permit scheduled breeding of mares during the physiological breeding season. To permit scheduled breeding, mares which are regularly cycling or which have active ovarian function should be given Altren® Solution 0.22% daily for 15 consecutive days, beginning 20 days before the date of the planned estrus. Ovulation will occur 5 to 7 days following the onset of estrus as expected for non- treated mares. Breeding should follow usual procedures for mares in estrus. Mares may be regulated and scheduled either individually or in groups.

CONTRAINDICATIONS:

Horses: Altren® Solution 0.22% is contraindicated in pregnant mares and in mares having a previous history of uterine inflammation (i.e. a Grade II or greater uterine biopsy result), or current uterine inflammations (i.e. acute, subacute or chronic endometritis). Altren® Solution 0.22% therapy may exacerbate an existing uterine inflammation into a fulminating uterine inflammation. The safety of this drug in pregnant mares has not been established. Various synthetic progestins, including altrenogest, when administered to rats during the embryonic stage of pregnancy at doses many fold greater than the recommended equine dose caused foetal anomalies, specifically of the female genitalia.

Swine: Altren® Solution 0.22% is contraindicated in gestating gilts or sows and is not to be administered to breeding boars since it could interfere with their fertility.

CAUTIONS:

Horses and Swine: The effect of this drug on post-treatment reproductive performance has not been fully documented. Swine: Over dosing may lead to a delay in the return to estrus. Under dosing may lead to a greater risk of cystic ovaries or failure of estrus suppression.

WARNINGS:

Horses: This drug is not to be administered to horses that are intended to be slaughtered for use in food.
Swine: Treated animals must not be slaughtered for use in food for at least 42 days after the latest treatment with this drug.

The following individuals should not handle this product (based upon the known effects of progestins used in humans on a chronic basis):
- Pregnant women or women who suspect they are pregnant.
- Women with known or suspected breast, uterine, or endometrial hormone-dependent cancer.
- Women with undiagnosed vaginal bleeding.
- Persons with thrombophlebitis or thromboembolic disorders or with a history of these events.
- Persons with cerebral-vascular or coronary-artery disease.
- Persons with known or suspected estrogen-dependent neoplasia.
- Persons with benign or malignant tumors which developed during the use of oral contraceptives or other estrogen-containing products.
- Persons with liver dysfunction or disease.
Altrenogest is readily absorbed by the skin. Avoid contact with skin or eyes and oral exposure. When handling this product, vinyl, neoprene or nitrile protective gloves must be worn.

Women of childbearing age should exercise extreme caution when handling this product. Accidental absorption could lead to a disruption of the menstrual cycle.

The following measures are recommended in case of accidental exposure:
- Skin Exposure: Wash immediately with soap and water.
- Eye Exposure: Immediately flush with plenty of water. Get medical attention.
- If Swallowed: Do not induce vomiting. The product contains an oil. Call a physician. Vomiting should be supervised by a physician because of possible pulmonary damage via aspiration of the oil base. Show the product label to the physician.

Effects of overexposure: There has been no human use of this product. The information in this section is extrapolated from data available on other products of the same pharmacological class that have been used in humans. Effects anticipated are due to the progestational activity of altrenogest. Acute effects after a single exposure are possible; however, continued daily exposure has the potential for more untoward effects such as disruption of the menstrual cycle, uterine or abdominal cramping, increased or decreased uterine bleeding, prolongation of pregnancy and headaches. The oil base may also cause complications if swallowed.

Keep out of reach of children.

STORAGE:

Store upright between 15 and 30°C. Protect fron freezing.

SUPPLY:

1 litre plastic bottle

PRINCIPAL DISPLAY PANEL - 1000 mL bottle label

IN 50-1642 rev 07/2021